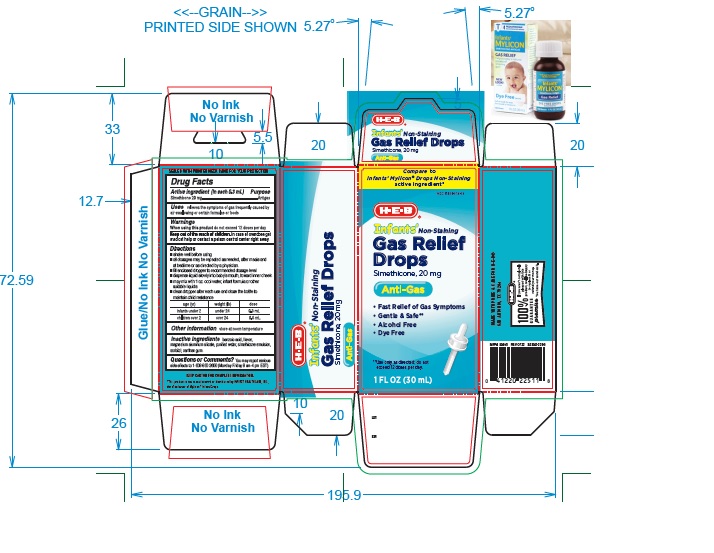 DRUG LABEL: Infants Non-staining Gas relief
NDC: 37808-014 | Form: SOLUTION/ DROPS
Manufacturer: H E B
Category: otc | Type: Human OTC Drug Label
Date: 20231204

ACTIVE INGREDIENTS: DIMETHICONE 20 mg/0.3 mL
INACTIVE INGREDIENTS: BENZOIC ACID; MAGNESIUM ALUMINUM SILICATE; WATER; SORBITOL; XANTHAN GUM

HEB Infants Gas Relief Drops

ACTIVE INGREDIENT (in each 0.3 mL)

Simethicone 20 mg

PURPOSE

Antigas

USE(S)

relieves the symptoms of gas frequently caused by air swallowing or certain formulas or foods

WARNINGS

When using this product do not exceed 12 doses per day

KEEP OUT OF REACH OF CHILDREN

In case of overdose, get medical help or contact a Poison Control Center right away.

DIRECTIONS

- shake well before using
- all dosages may be repeated as needed, after meals and at bedtime or as directed by a physician.
- fill enclosed dropper to recommended dosage level
- dispense liquid slowly into baby's mouth, toward the inner cheek
- may mix with 1 oz. of cool water, infant formula or other suitable liquids.
- clean dropper after each use and close the bottle to maintain child resistance

age (yr) | weight (lb) | dose
infants under 2 | under 24 | 0.3 mL
children over 2 | over 24 | 0.6 mL

OTHER INFORMATION

store at room temperature

INACTIVE INGREDIENT SECTION

benzoic acid, flavor, magnesium aluminum silicate, purified water, simethicone emulsion, sorbitol, xanthan gum.

QUESTIONS?

You may report serious side effects to 1-609-860-2600 (Monday-Friday 8 am-4 pm EST).

PRINCIPAL DISPLAY PANEL

Compare to Infants' Mylicon® Drops Non-Staining active ingredient*

NDC 37808-014-09

HEB

Infants' Non-Staining

Gas Relief

Drops

simethicone 20 mg

Anti-Gas

- Fast Relief of Gas Symptoms
- No Artificial flavor
- Gentle & Safe**
- Alcohol Free
- Dye free

**Use only as directed, do not exceed more than 12 doses per day.

1 FL OZ (30 mL)